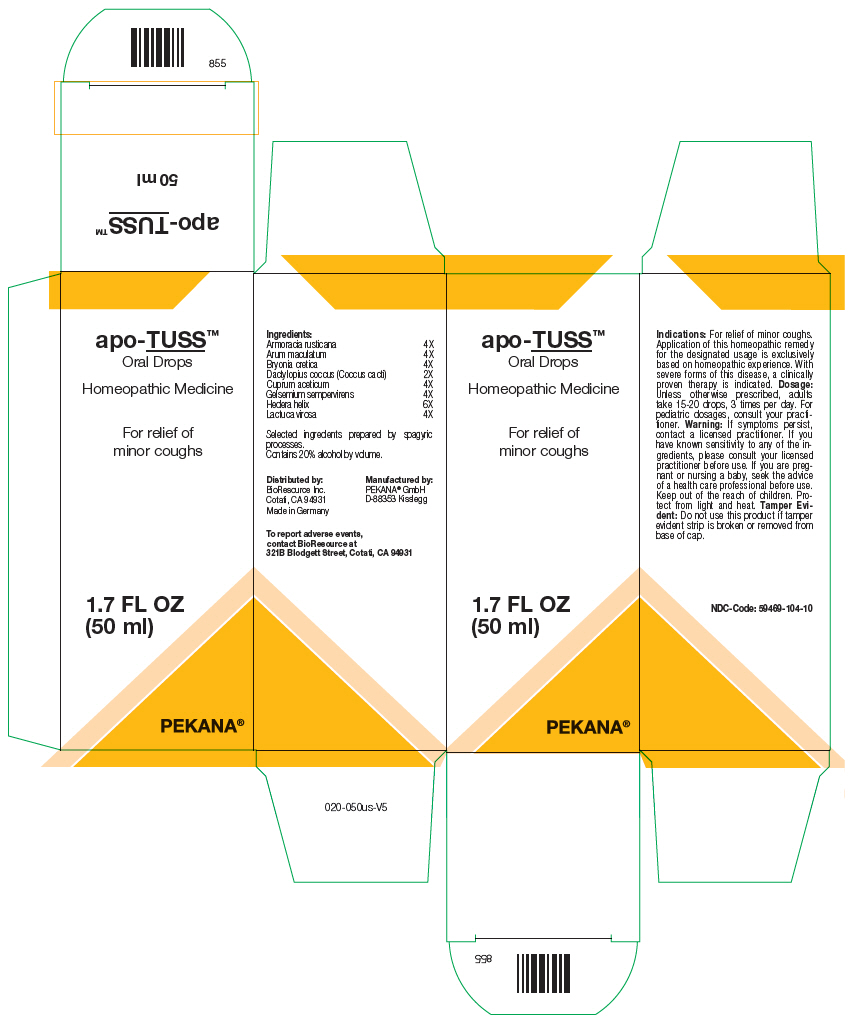 DRUG LABEL: apo-TUSS
NDC: 59469-104 | Form: SOLUTION/ DROPS
Manufacturer: PEKANA Naturheilmittel GmbH
Category: homeopathic | Type: HUMAN OTC DRUG LABEL
Date: 20221206

ACTIVE INGREDIENTS: Arum Maculatum Root 4 [hp_X]/50 mL; Bryonia Dioica Root 4 [hp_X]/50 mL; Protortonia Cacti 2 [hp_X]/50 mL; Cupric Acetate 4 [hp_X]/50 mL; Gelsemium sempervirens Root 4 [hp_X]/50 mL; Hedera helix Flowering Twig 6 [hp_X]/50 mL; LACTUCA VIROSA WHOLE 4 [hp_X]/50 mL; Horseradish 4 [hp_X]/50 mL
INACTIVE INGREDIENTS: Water; Alcohol

apo-TUSS™

ACTIVE INGREDIENT

Ingredients:
Armoracia rusticana | 4X
Arum maculatum | 4X
Bryonia cretica | 4X
Dactylopius coccus (Coccus cacti) | 2X
Cuprum aceticum | 4X
Gelsemium sempervirens | 4X
Hedera helix | 6X
Lactuca virosa | 4X

Selected ingredients prepared by spagyric processes.

INACTIVE INGREDIENT

Contains 20% alcohol by volume.

Indications

PURPOSE

For relief of minor coughs. Application of this homeopathic remedy for the designated usage is exclusively based on homeopathic experience. With severe forms of this disease, a clinically proven therapy is indicated.

Dosage

Unless otherwise prescribed, adults take 15-20 drops, 3 times per day. For pediatric dosages, consult your practitioner.

Warning

If symptoms persist, contact a licensed practitioner. If you have known sensitivity to any of the ingredients, please consult your licensed practitioner before use. If you are pregnant or nursing a baby, seek the advice of a health care professional before use.

Keep out of the reach of children.

STORAGE AND HANDLING

Protect from light and heat.

Tamper Evident

Do not use this product if tamper evident strip is broken or removed from base of cap.

QUESTIONS

To report adverse events, contact BioResource at 321B Blodgett Street, Cotati, CA 94931

Distributed by:
BioResource Inc.
Cotati, CA 94931

Manufactured by:
PEKANA® GmbH
D-88353 Kisslegg

PRINCIPAL DISPLAY PANEL - 50 ml Bottle Box

apo-TUSS™
Oral Drops

Homeopathic Medicine

For relief of
minor coughs

1.7 FL OZ
(50 ml)

PEKANA®